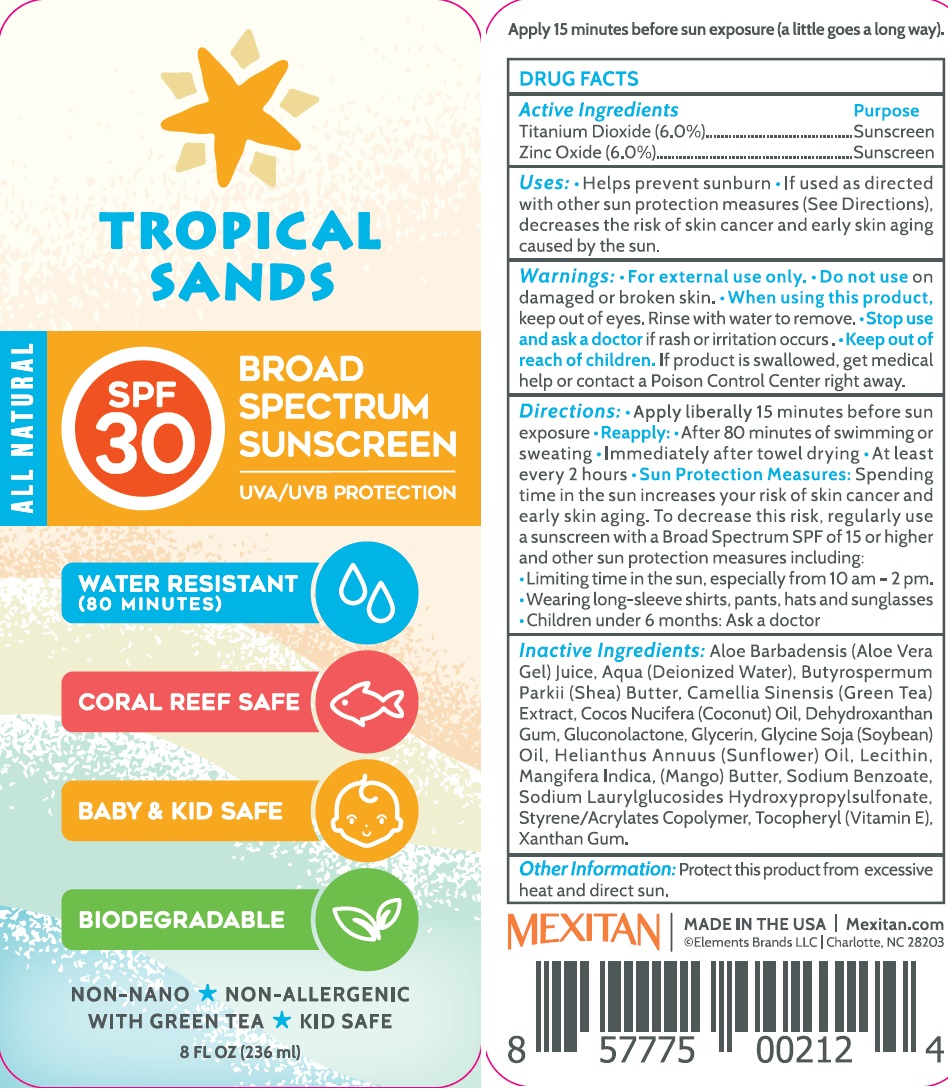 DRUG LABEL: Tropical Sands SPF-30 Broad Spectrum Sunscreen
NDC: 71221-796 | Form: CREAM
Manufacturer: Elements Brands, Inc.
Category: otc | Type: HUMAN OTC DRUG LABEL
Date: 20231111

ACTIVE INGREDIENTS: TITANIUM DIOXIDE 60 mg/1 mL; ZINC OXIDE 60 mg/1 mL
INACTIVE INGREDIENTS: ALOE VERA LEAF; WATER; GREEN TEA LEAF; COCONUT OIL; DEHYDROXANTHAN GUM; GLUCONOLACTONE; GLYCERIN; SOYBEAN OIL; HELIANTHUS ANNUUS FLOWERING TOP; MANGO; SODIUM BENZOATE; .ALPHA.-TOCOPHEROL; XANTHAN GUM

Tropical Sands SPF-30 Broad Spectrum Sunscreen

Active Ingredients

Titanium Dioxide (6.0%)

Zinc Oxide (6.0%)

Purpose

Sunscreen

Uses:

• Helps prevent sunburn • If used as directed with other sun protection measures (See Directions), decreases the risk of skin cancer and early skin aging caused by the sun.

Warnings:

• For external use only.

Do not use

on damaged or broken skin.

When using this product

keep out of eyes. Rinse with water to remove.

Stop use and ask a doctor

if rash or irritation occurs.

Keep out of reach of children.

If product is swallowed, get medical help or contact a Poison Control Center right away.

Directions:

• Apply liberally 15 minutes before sun exposure • Reapply: • After 80 minutes of swimming or sweating • Immediately after towel drying • At least every 2 hours • Spending time in the sun increases your risk of skin cancer and early skin aging. To decrease this risk, regularly use a sunscreen with a Broad Spectrum SPF of 15 or higher and other sun protection measures including: •Limit time in the sun, especially from 10 am – 2 pm. •Wear long sleeve shirts, pants, hats and sunglasses. •For children under 6 months: consult a physician. Sun Protection Measures:

Inactive Ingredients:

Aloe Barbadensis Leaf (Aloe Vera Gel) Juice, Aqua (Deionized Water), Butyrospermum Parkii (Shea) Butter, Camellia Sinensis (Green Tea) Extract, Cocos Nucifera (Coconut) Oil, Dehydroxanthan Gum, Gluconolactone, Glycerin, Glycine Soja (Soybean) Oil, Helianthus Annuus (Sunflower) Oil, Lecithin, Mangifera Indica (Mango) Butter, Sodium Benzoate, Sodium Laurylglucosides Hydroxypropylsulfonate, Styrene/Acrylates Copolymer, Tocopheryl (VItamin E), Xanthan Gum

Other Information:

Protect this product from excessive heat and direct sun.